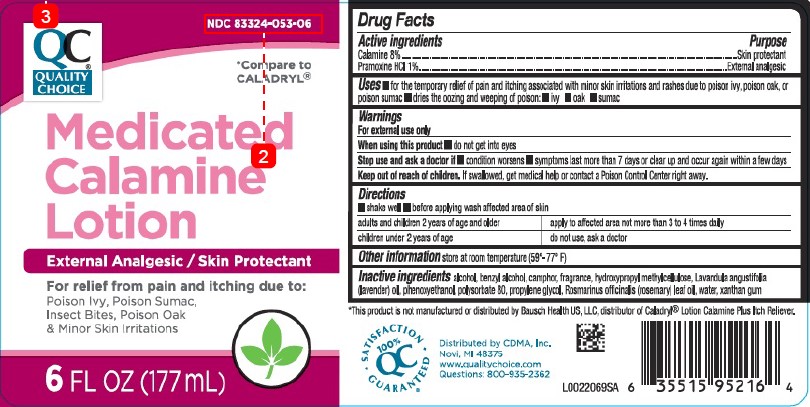 DRUG LABEL: Calamine
NDC: 83324-053 | Form: LOTION
Manufacturer: Chain Drug Marketing Association
Category: otc | Type: HUMAN OTC DRUG LABEL
Date: 20260227

ACTIVE INGREDIENTS: FERRIC OXIDE RED 80 mg/1 mL; PRAMOXINE HYDROCHLORIDE 10 mg/1 mL
INACTIVE INGREDIENTS: ALCOHOL; BENZYL ALCOHOL; CAMPHOR (NATURAL); HYPROMELLOSE, UNSPECIFIED; LAVENDER OIL; PHENOXYETHANOL; POLYSORBATE 80; PROPYLENE GLYCOL; ROSEMARY OIL; WATER; XANTHAN GUM

Quality Choice 336.003/336AG
Medicated Calamine Lotion

Active ingredients

Calamine 8%

Pramoxine HCl 1%

Purpose

Skin protectant

External analgesic

Uses

- for the temporary relief of pain and itching associated with minot skin irritations and rashes due to poison ivy, poison oak, or poison sumac
- dries the oozing and weeping of poison:
- ivy
- oak
- sumac

Warnings

For external use only

When using this product

- do not get into eyes

Stop use and ask a doctor

- condition worsens
- symptoms last more than 7 days or clean up and occur again within a few days

Keep out of reach of children

If swallowed, get medical help or contact a Poison Control Center right away.

Directions

- shake well
- before applying was affected are of skin

Adults and children 2 years of age and older - apply to affected area not more than 3 to 4 times daily

Children under 2 years of age - do not use, ask a doctor

Other information

store at room temperature (59°-77°F)

Inactive ingredients

alcohol, benzyl alcohol, camphor, fragrance, hydroxypropyl methylcellulose, Lavandula angustifolia (lavender) oil, phenoxyethanol, polysorbate 80, propylene glycol, Rosmarinus officinalis (rosemary) leaf oil, water, xanthan gum

Disclaimer

*This product is not manufactured or distributed by Bausch Health US, LLC, distributor of Caladryl Lotion Calamine Plus Itch Reliever.

ADVERSE REACTION

Distributed by CDMA, Inc.

Novi, MI 48375

www.qualitychoice.com

Questions: 800-935-2362

SATISFACTION GUARANTEED

100% QC

PRINCIPAL DISPLAY PANEL

NDC 83324-053-06

QC

QUALITY CHOICE

*Compare to CALADRYL

Medicated

Calamine

Lotion

External Analgesic/Skin Protectant

For relief from pain and itching due to:

Poison Ivy, Poison Sumac, Insect Bites, Poison Oak & Minor Skin Irritations

6 FL OZ (177 mL)